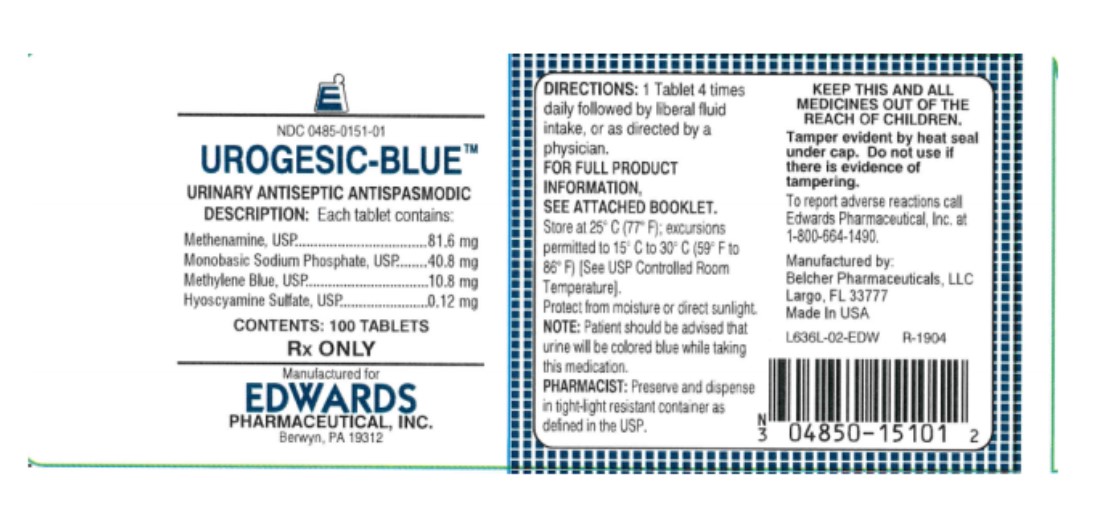 DRUG LABEL: UROGESIC BLUE
NDC: 0485-0151 | Form: TABLET, COATED
Manufacturer: EDWARDS PHARMACEUTICALS, INC.
Category: prescription | Type: HUMAN PRESCRIPTION DRUG LABEL
Date: 20250819

ACTIVE INGREDIENTS: METHENAMINE 81.6 mg/1 1; SODIUM PHOSPHATE, MONOBASIC 40.8 mg/1 1; METHYLENE BLUE 10.8 mg/1 1; HYOSCYAMINE SULFATE 0.12 mg/1 1
INACTIVE INGREDIENTS: CELLULOSE, MICROCRYSTALLINE; MANNITOL; CROSCARMELLOSE SODIUM; MAGNESIUM STEARATE

UROGESIC-BLUE™

Rx Only

Description

Each tablet contains:

 | Methenamine, USP | 81.6 mg
 | Monobasic Sodium Phosphate, USP | 40.8 mg
 | Methylene Blue, USP | 10.8 mg
 | Hyoscyamine Sulfate, USP | 0.12 mg

Inactive Ingredients include: microcrystalline cellulose, NF, mannitol, USP, croscarmellose sodium, NF, magnesium stearate, NF and lake blend blue.

HYOSCYAMINE SULFATE is an alkaloid of belladonna. Exists as a white crystalline powder. Affected by light It is very soluble in water; freely soluble in alcohol; practically insoluble in ether.

METHENAMINE exists as colorless, lustrous crystals or white crystalline powder. Its solutions are alkaline to litmus. Freely soluble in water; soluble in alcohol and in chloroform.

METHYLENE BLUE exists as dark green crystals. It is soluble in water and in chloroform; sparingly soluble in alcohol.

MONOBASIC SODIUM PHOSPHATE exists as a white crystalline powder. Its solutions are acidic to litmus. It is freely soluble in water and practically insoluble in alcohol.

CLINICAL PHARMACOLOGY

HYOSCYAMINE is a parasympatholytic which relaxes smooth muscles and thus produces an antispasmodic effect. It is well absorbed from the gastrointestinal tract and is rapidly distributed throughout body tissues. Most is excreted in the urine within 12 hours, 13% to 50% being unchanged. Its biotransformation is hepatic. Its protein binding is moderate.

METHENAMINE degrades in an acidic urine environment releasing formaldehyde which provides bactericidal or bacteriostatic action. It is well absorbed from the gastrointestinal tract. 70% to 90% reaches the urine unchanged at which point it is hydrolyzed if the urine is acidic. Within 24 hours it is almost completely (90%) excreted; of this amount at pH 5, approximately 20% is formaldehyde. Protein binding: some formaldehyde is bound to substances in the urine and surrounding tissues. Methenamine is freely distributed to body tissue and fluids but is not clinically significant as it does not hydrolyze at pH greater than 6.8.

METHYLENE BLUE possesses weak antiseptic properties. It is well absorbed in the gastrointestinal tract and is rapidly reduced to leukomethylene blue which is stabilized in some combination form in the urine. 75% is excreted unchanged.

MONOBASIC SODIUM PHOSPHATE helps to maintain an acid pH in the urine necessary for the degradation of methenamine.

INDICATIONS AND USAGE

UROGESIC-BLUE™ is indicated for the treatment of symptoms of irritative voiding. Indicated for the relief of local symptoms, such as hypermotility which accompany lower urinary tract infections and as antispasmodic. Indicated for the relief of urinary tract symptoms caused by diagnostic procedures.

CONTRAINDICATIONS

UROGESIC-BLUE™ is contraindicated in patients with a hypersensitivity to any of the ingredients. Risk-benefit should be considered when the following medical problems exist: Cardiac disease (especially cardiac arrythmias, congestive heart failure, coronary heart disease, mitral stenosis); gastrointestinal tract obstructive disease; glaucoma; myasthenia gravis; acute urinary retention may be precipitated in obstructive uropathy (such as bladder neck obstruction due to prostatic hypertrophy).

WARNINGS

Do not exceed recommended dosage. If rapid pulse, dizziness, or blurring of vision occurs discontinue use immediately.

PRECAUTIONS

Cross sensitivity and/or related problems

patients intolerant of belladonna alkaloids may be intolerant of this medication also.

Pregnancy/Reproduction

(Pregnancy Category C)

hyoscyamine and methenamine cross the placenta. Studies have not been done in animals or humans. It is not known whether UROGESIC-BLUE™ tablets cause fetal harm when administered to a pregnant woman or can affect reproduction capacity. UROGESIC-BLUE™ tablets should be given to a pregnant woman only if clearly needed.

Breast-feeding

problems in humans have not been documented; however, methenamine and traces of hyoscyamine are excreted in breast milk.

Prolonged use

there have been no studies to establish the safety of prolonged use in humans. No known long-term animal studies have been performed to evaluate carcinogenic potential.

Pediatric

infants and young children are especially susceptible to the toxic effect of the belladonna alkaloids.

Geriatric

use with caution in elderly patients as they may respond to usual doses of hyoscyamine with excitement, agitation, drowsiness, or confusion.

Drug Interactions

because of this product's effect on gastrointestinal motility and gastric emptying, it may decrease the absorption of other oral medications during concurrent use such as: urinary alkalizers; thiazide diuretics (may cause the urine to become alkaline reducing the effectiveness of methenamine by inhibiting its conversion to formaldehyde); antimuscarinics (concurrent use may intensify antimuscarinic effects of hyoscyamine because of secondary antimuscarinic activities of these medications); antacids/antidiarrheals (may reduce absorption of hyoscyamine, concurrent use with antacids may cause urine to become alkaline reducing effectiveness of methenamine by inhibiting its conversion to formaldehyde) doses of these medications should be spaced 1 hour apart from doses of hyoscyamine; antimyasthenics (concurrent use with hyoscyamine may further reduce intestinal motility); ketoconazole (patients should be advised to take this combination at least 2 hours after ketoconazole); monoamine oxidase (MAO) Inhibitors (concurrent use may intensify antimuscarinic side effects, opoid (narcotic) analgesics may result in increased risk of severe constipation); sulfonamides (these drugs may precipitate with formaldehyde in the urine, increasing the danger of crystalluria).

Patients should be advised that the urine may become blue to blue green and the feces may be discolored as a result of the excretion of methylene blue.

ADVERSE REACTIONS

Cardiovascular – rapid pulse, flushing

Central Nervous System – blurred vision, dizziness

Respiratory – shortness of breath or troubled breathing

Genitourinary – difficulty micturition, acute urinary retention

Gastrointestinal – dry mouth, nausea/vomiting

DRUG ABUSE AND DEPENDENCE

A dependence on the use of UROGESIC-BLUE™ has not been reported and due to the nature of its ingredients, abuse of UROGESIC-BLUE™ is not expected.

OVERDOSAGE

Emesis or gastric lavage. Slow intravenous administration of physostigmine in doses of 1 mg to 4 mg (0.5 mg to 1 mg in children), repeated as needed in one to two hours to reverse severe antimuscarinic symptoms. Administration of small doses of diazepam to control excitement and seizures. Artificial respiration with oxygen if needed for respiratory depression. Adequate hydration. Symptomatic treatment as necessary.

DOSAGE AND ADMINISTRATION

Adults

One tablet orally 4 times per day followed by liberal fluid intake.

Older Children

Dosage must be individualized by physician. Not recommended for use in children up to 6 years of age.

HOW SUPPLIED

UROGESIC-BLUE™ are light blue to blue, oval, biconvex tablets debossed with "ED UB" with scoreline on one side and plain on the other side. Supplied in bottles of 100 tablets (NDC 0485-0151-01).

CAUTION

RX ONLY

STORAGE

Store at 25° C (77° F); excursions permitted to 15° C to 30° C (59° F to 86° F) (See USP Controlled Room Temperature). Keep container tightly closed.

Manufactured for:
Edwards Pharmaceutical, Inc.
111 W. Mulberry St. Ripley, Mississippi 38663

Manufactured by:
Belcher Pharmaceuticals, LLC
Largo, FL 33777

May 2011 R-0110B

PRINCIPAL DISPLAY PANEL - 100 count Tablet Bottle Label

NEW
FORMULATION

NDC 0485-0151-01

UROGESIC-BLUE™

URINARY ANTISEPTIC
ANTISPASMODIC

DESCRIPTION:

Each tablet contains:

Methenamine, USP 81.6 mg
Monobasic Sodium Phosphate, USP 40.8 mg
Methylene Blue, USP 10.8 mg
Hyoscyamine Sulfate, USP 0.12 mg

CONTENTS: 100 TABLETS

RX ONLY

Manufactured for
EDWARDS
PHARMACEUTICAL, INC.
Berwyn, PA